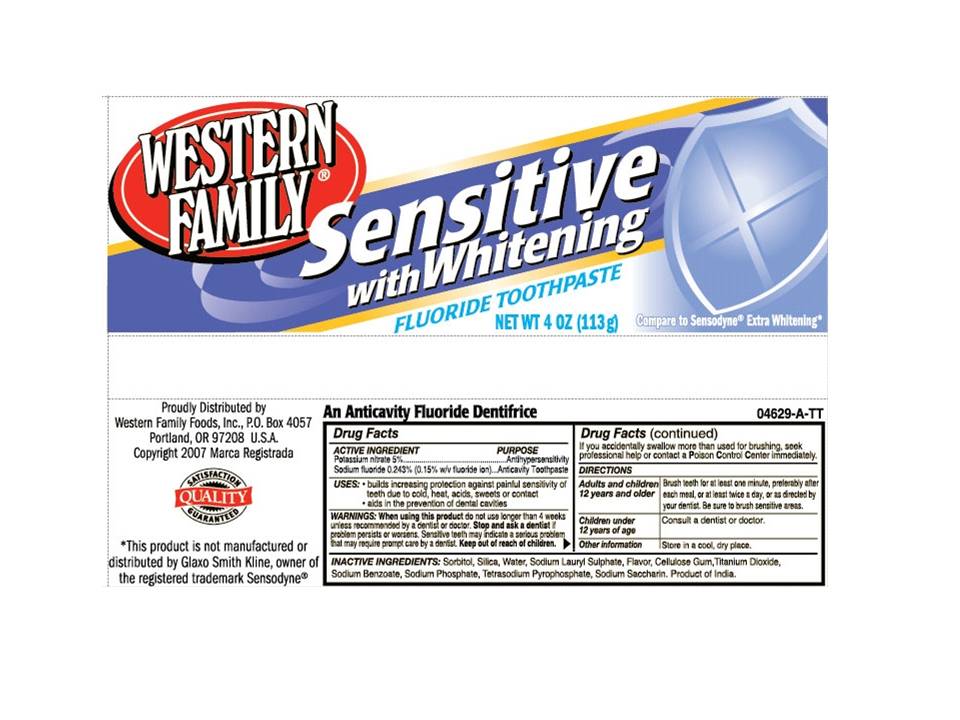 DRUG LABEL: Western Family Sensitive Whitening Fluoride
NDC: 55312-158 | Form: PASTE, DENTIFRICE
Manufacturer: Western Family Food, Inc.
Category: otc | Type: HUMAN OTC DRUG LABEL
Date: 20110218

ACTIVE INGREDIENTS: POTASSIUM NITRATE 5 mg/1 g; SODIUM FLUORIDE 2.43 mg/1 g
INACTIVE INGREDIENTS: SORBITOL; SILICON DIOXIDE; WATER; SODIUM LAURYL SULFATE; CARBOXYMETHYLCELLULOSE SODIUM; TITANIUM DIOXIDE; SODIUM BENZOATE; SODIUM PHOSPHATE; SODIUM PYROPHOSPHATE; SACCHARIN SODIUM

Western Family Sensitive Whitening Fluoride Toothpaste

Active Ingredient

Potassium Nitrate 5%..................Antihypersensitivity

Sodium Fluoride 0.243% (0.15% w/v fluoride ion).......Anticavity Toothpaste

USE

- builds increasing protection against painful sensitivity of teeth due to cold, heat, acids, sweets or contact
- aids in the prevention of dental cavities

When using this product do not use longer than 4 weeks unless recommended by a dentist or doctor. Stop and ask a dentist if problem persists or worsens. Sensitive teeth may indicate a serious problem that may require prompt care by a dentist. Keep out of reach of children.

Directions

Adults and children Brush teeth for at least one minute, preferably after
12 years and older each meal, or at least twice a day, or as directed by your dentist.
Be sure to brush sensitive areas.

Children under Consult a dentist or doctor.
12 years of age

Other information Store in a cool, dry place.

Inactive Ingredients

Sorbitol, Silica, Water, Sodium Lauryl Sulphate, Flavor, Cellulose gum, Titanium Dioxide, Sodium Benzoate, Sodium Phosphate, Tetrasodium Pyrophosphate, Sodium Saccharin